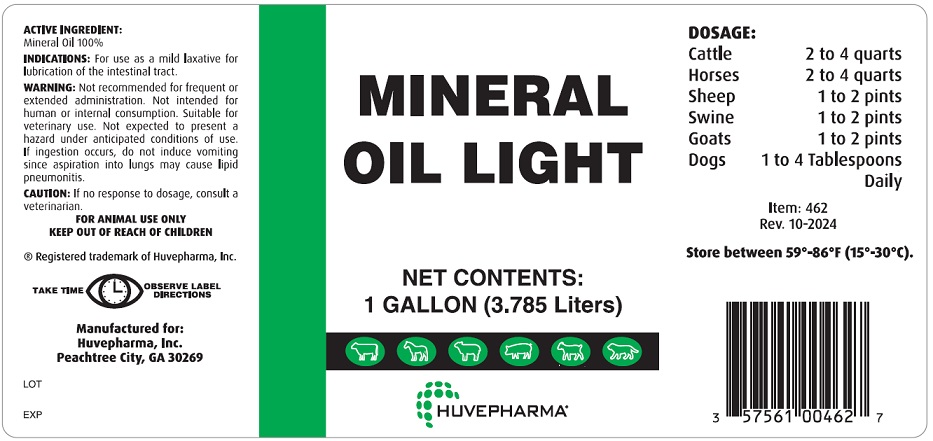 DRUG LABEL: Mineral Oil Light
NDC: 23243-0448 | Form: LIQUID
Manufacturer: Huvepharma, Inc
Category: animal | Type: OTC ANIMAL DRUG LABEL
Date: 20251126

ACTIVE INGREDIENTS: LIGHT MINERAL OIL 3.785 L/3.785 L

WARNINGS AND PRECAUTIONS

MINERAL OIL LIGHT

ACTIVE INGREDIENTS:

Mineral Oil 100%

INDICATION: For use as a mild laxative for lubrication of the intestinal tract.

WARNING: Not recommended for frequent repeated or extended administration. Not intended for human or internal consumption. Suitable for veterinary use. Not expected to present a hazard under anticipated conditions of use. If ingestion occurs, do not induce vomiting since aspiration into lungs may cause lipid pneumonitis.

CAUTION: If no response to dosage, consult a veterinarian.

FOR ANIMAL USE ONLY.

KEEP OUT OF REACH OF CHILDREN.

DOSAGE:

Cattle 2 to 4 quarts

Horses 2 to 4 quarts

Sheep 1 to 2 pints

Swine 1 to 2 pints

Goats 1 to 2 pints

Dogs 1 to 4 Tablespoons

Daily

Store Between 59-89°F (15-30°C)

Manufactured for:

Huvepharma, Inc.

Peachtree City, GA 30269